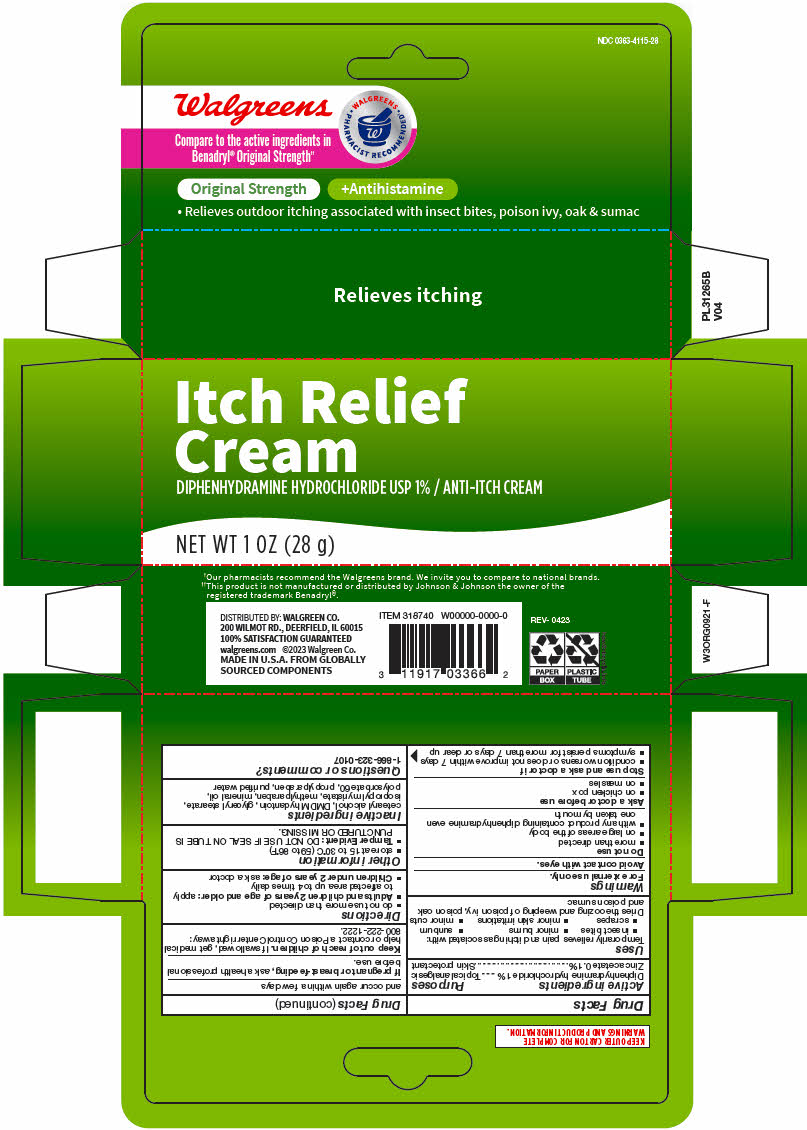 DRUG LABEL: Walgreens Original Strength Anti Itch
NDC: 0363-4115 | Form: CREAM
Manufacturer: Walgreen Company
Category: otc | Type: HUMAN OTC DRUG LABEL
Date: 20260128

ACTIVE INGREDIENTS: DIPHENHYDRAMINE HYDROCHLORIDE 1 g/100 g; ZINC ACETATE 0.1 g/100 g
INACTIVE INGREDIENTS: METHYLPARABEN; POLYOXYL 40 STEARATE TYPE I; PROPYLENE GLYCOL; PROPYLPARABEN; WATER; STEARYL ALCOHOL

Walgreens Original Strength Anti Itch

Drug Facts

ACTIVE INGREDIENT

PURPOSE

Active ingredients | Purposes
Diphenhydramine hydrochloride 1% | Topical analgesic
Zinc acetate 0.1% | Skin protectant

Uses

Temporarily relieves pain and itching associated with:

- insect bites
- minor burns
- sunburn
- scrapes
- minor skin irritations
- minor cuts

Dries the oozing and weeping of poison ivy, poison oak and poison sumac

Warnings

For external use only.

Avoid contact with eyes.

Do not use

- more than directed
- on large areas of the body
- with any product containing diphenhydramine even one taken by mouth

Ask a doctor before use

- on chicken pox
- on measles

Stop use and ask a doctor if

- condition worsens or does not improve within 7 days
- symptoms persist for more than 7 days or clear up and occur again within a few days

PREGNANCY OR BREAST FEEDING

If pregnant or breast-feeding, ask a health professional before use.

Keep out of reach of children. If swallowed, get medical help or contact a Poison Control Center right away: 800-222-1222.

Directions

- do not use more than directed
- Adults and children 2 years of age and older: apply to affected area up to 4 times daily
- Children under 2 years of age: ask a doctor

Other information

- store at 15 to 30°C (59 to 86°F)
- Tamper Evident: DO NOT USE IF SEAL ON TUBE IS PUNCTURED OR MISSING.

Inactive ingredients

cetearyl alcohol (and) polysorbate 60, DMDM hydantoin, glyceryl stearate, isopropyl myristate, methylparaben, mineral oil, propylparaben, purified water

Questions or comments?

1-866-323-0107

DISTRIBUTED BY: WALGREEN CO.
200 WILMOT RD., DEERFIELD, IL 60015

PRINCIPAL DISPLAY PANEL - 28 g Tube Carton

Itch Relief
Cream
DIPHENHYDRAMINE HYDROCHLORIDE USP 1% / ANTI-ITCH CREAM

NET WT 1 OZ (28 g)